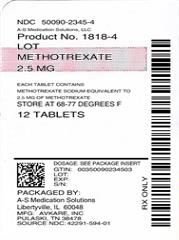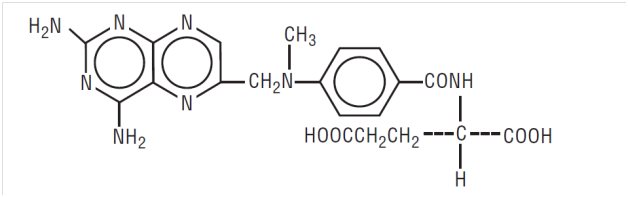 DRUG LABEL: Methotrexate
NDC: 50090-2345 | Form: TABLET
Manufacturer: A-S Medication Solutions
Category: prescription | Type: HUMAN PRESCRIPTION DRUG LABEL
Date: 20180823

ACTIVE INGREDIENTS: METHOTREXATE SODIUM 2.5 mg/1 1
INACTIVE INGREDIENTS: HYPROMELLOSE, UNSPECIFIED; ANHYDROUS LACTOSE; MAGNESIUM STEARATE; MICROCRYSTALLINE CELLULOSE; POLYETHYLENE GLYCOL, UNSPECIFIED; STARCH, CORN; PROPYLENE GLYCOL; SODIUM CARBONATE MONOHYDRATE; TALC

Methotrexate Tablets USP

WARNINGS

METHOTREXATE SHOULD BE USED ONLY BY PHYSICIANS WHOSE KNOWLEDGE AND EXPERIENCE INCLUDE THE USE OF ANTIMETABOLITE THERAPY BECAUSE OF THE POSSIBILITY OF SERIOUS TOXIC REACTIONS (WHICH CAN BE FATAL):

METHOTREXATE SHOULD BE USED ONLY IN LIFE THREATENING NEOPLASTIC DISEASES, OR IN PATIENTS WITH PSORIASIS OR RHEUMATOID ARTHRITIS WITH SEVERE, RECALCITRANT, DISABLING DISEASE WHICH IS NOT ADEQUATELY RESPONSIVE TO OTHER FORMS OF THERAPY.

DEATHS HAVE BEEN REPORTED WITH THE USE OF METHOTREXATE IN THE TREATMENT OF MALIGNANCY, PSORIASIS, AND RHEUMATOID ARTHRITIS.

PATIENTS SHOULD BE CLOSELY MONITORED FOR BONE MARROW, LIVER, LUNG AND KIDNEY TOXICITIES. (See PRECAUTIONS.)

PATIENTS SHOULD BE INFORMED BY THEIR PHYSICIAN OF THE RISKS INVOLVED AND BE UNDER A PHYSICIAN’S CARE THROUGHOUT THERAPY.

1. Methotrexate has been reported to cause fetal death and/or congenital anomalies. Therefore, it is not recommended for women of childbearing potential unless there is clear medical evidence that the benefits can be expected to outweigh the considered risks. Pregnant women with psoriasis or rheumatoid arthritis should not receive methotrexate. (See CONTRAINDICATIONS.)
2. Methotrexate elimination is reduced in patients with impaired renal function, ascites, or pleural effusions. Such patients require especially careful monitoring for toxicity, and require dose reduction or, in some cases, discontinuation of methotrexate administration.
3. Unexpectedly severe (sometimes fatal) bone marrow suppression, aplastic anemia, and gastrointestinal toxicity have been reported with concomitant administration of methotrexate (usually in high dosage) along with some non-steroidal anti-inflammatory drugs (NSAIDs). (See PRECAUTIONS, Drug Interactions.)
4. Methotrexate causes hepatotoxicity, fibrosis and cirrhosis, but generally only after prolonged use. Acutely, liver enzyme elevations are frequently seen. These are usually transient and asymptomatic, and also do not appear predictive of subsequent hepatic disease. Liver biopsy after sustained use often shows histologic changes, and fibrosis and cirrhosis have been reported; these latter lesions may not be preceded by symptoms or abnormal liver function tests in the psoriasis population. For this reason, periodic liver biopsies are usually recommended for psoriatic patients who are under long-term treatment. Persistent abnormalities in liver function tests may precede appearance of fibrosis or cirrhosis in the rheumatoid arthritis population. (See PRECAUTIONS, Organ System Toxicity, Hepatic.)
5. Methotrexate-induced lung disease is a potentially dangerous lesion, which may occur acutely at any time during therapy and which has been reported at doses as low as 7.5 mg/week. It is not always fully reversible. Pulmonary symptoms (especially a dry, nonproductive cough) may require interruption of treatment and careful investigation.
6. Diarrhea and ulcerative stomatitis require interruption of therapy; otherwise, hemorrhagic enteritis and death from intestinal perforation may occur.
7. Malignant lymphomas, which may regress following withdrawal of methotrexate, may occur in patients receiving low-dose methotrexate and, thus, may not require cytotoxic treatment. Discontinue methotrexate first and, if the lymphoma does not regress, appropriate treatment should be instituted.
8. Like other cytotoxic drugs, methotrexate may induce “tumor lysis syndrome” in patients with rapidly growing tumors. Appropriate supportive and pharmacologic measures may prevent or alleviate this complication.
9. Severe, occasionally fatal, skin reactions have been reported following single or multiple doses of methotrexate. Reactions have occurred within days of oral, intramuscular, intravenous, or intrathecal methotrexate administration. Recovery has been reported with discontinuation of therapy. (See PRECAUTIONS, Organ System Toxicity, Skin).
10. Potentially fatal opportunistic infections, especially Pneumocystis carinii pneumonia, may occur with methotrexate therapy.
11. Methotrexate given concomitantly with radiotherapy may increase the risk of soft tissue necrosis and osteonecrosis.

DESCRIPTION

Methotrexate, USP (formerly Amethopterin) is an antimetabolite used in the treatment of certain neoplastic diseases, severe psoriasis, and adult rheumatoid arthritis. Chemically methotrexate is N-[4-[[(2,4-diamino-6-pteridinyl)methyl]methylamino]benzoyl]-L-glutamic acid. The structural formula is:

C20H22N8O5 M.W. 454.45

Methotrexate Tablets USP for oral administration, are available in bottles of 36 and 100. Methotrexate Tablets USP contain an amount of methotrexate sodium equivalent to 2.5 mg of methotrexate, USP.

Inactive Ingredients: Hydroxypropyl methylcellulose, lactose anhydrous, magnesium stearate, microcrystalline cellulose, polyethylene glycol, pregelatinized corn starch, propylene glycol, sodium carbonate monohydrate and talc.

CLINICAL PHARMACOLOGY

Methotrexate inhibits dihydrofolic acid reductase. Dihydrofolates must be reduced to tetrahydrofolates by this enzyme before they can be utilized as carriers of one-carbon groups in the synthesis of purine nucleotides and thymidylate. Therefore, methotrexate interferes with DNA synthesis, repair, and cellular replication. Actively proliferating tissues such as malignant cells, bone marrow, fetal cells, buccal and intestinal mucosa, and cells of the urinary bladder are in general more sensitive to this effect of methotrexate. When cellular proliferation in malignant tissues is greater than in most normal tissues, methotrexate may impair malignant growth without irreversible damage to normal tissues.

The mechanism of action in rheumatoid arthritis is unknown; it may affect immune function. Two reports describe in vitro methotrexate inhibition of DNA precursor uptake by stimulated mononuclear cells, and another describes in animal polyarthritis partial correction by methotrexate of spleen cell hyporesponsiveness and suppressed IL 2 production. Other laboratories, however, have been unable to demonstrate similar effects. Clarification of methotrexate’s effect on immune activity and its relation to rheumatoid immunopathogenesis await further studies.

In patients with rheumatoid arthritis, effects of methotrexate on articular swelling and tenderness can be seen as early as 3 to 6 weeks. Although methotrexate clearly ameliorates symptoms of inflammation (pain, swelling, stiffness), there is no evidence that it induces remission of rheumatoid arthritis nor has a beneficial effect been demonstrated on bone erosions and other radiologic changes which result in impaired joint use, functional disability, and deformity.

Most studies of methotrexate in patients with rheumatoid arthritis are relatively short term (3 to 6 months). Limited data from long-term studies indicate that an initial clinical improvement is maintained for at least two years with continued therapy.

In psoriasis, the rate of production of epithelial cells in the skin is greatly increased over normal skin. This differential in proliferation rates is the basis for the use of methotrexate to control the psoriatic process.

In a 6-month, double-blind, placebo-controlled trial of 127 pediatric patients with juvenile rheumatoid arthritis (JRA) (mean age, 10.1 years; age range 2.5 to 18 years, mean duration of disease, 5.1 years) on background non-steroidal anti-inflammatory drugs (NSAIDs) and/or prednisone, methotrexate given weekly at an oral dose of 10 mg/m^2 provided significant clinical improvement compared to placebo as measured by either the physician’s global assessment, or by a patient composite (25% reduction in the articular-severity score plus improvement in parent and physician global assessments of disease activity.) Over two-thirds of the patients in this trial had polyarticular-course JRA, and the numerically greatest response was seen in this subgroup treated with 10 mg/m^2/wk methotrexate. The overwhelming majority of the remaining patients had systemic-course JRA. All patients were unresponsive to NSAIDs; approximately one-third were using low dose corticosteroids. Weekly methotrexate at a dose of 5 mg/m^2 was not significantly more effective than placebo in this trial.

Pharmacokinetics

Absorption - In adults, oral absorption appears to be dose dependent. Peak serum levels are reached within one to two hours. At doses of 30 mg/m^2 or less, methotrexate is generally well absorbed with a mean bioavailability of about 60%. The absorption of doses greater than 80 mg/m^2 is significantly less, possibly due to a saturation effect.

In leukemic pediatric patients, oral absorption of methotrexate also appears to be dose dependent and has been reported to vary widely (23% to 95%). A twenty fold difference between highest and lowest peak levels (Cmax: 0.11 to 2.3 micromolar after a 20 mg/m^2 dose) has been reported. Significant interindividual variability has also been noted in time to peak concentration (Tmax: 0.67 to 4 hrs after a 15 mg/m^2 dose) and fraction of dose absorbed. The absorption of doses greater than 40 mg/m^2 has been reported to be significantly less than that of lower doses. Food has been shown to delay absorption and reduce peak concentration. Methotrexate is generally completely absorbed from parenteral routes of injection. After intramuscular injection, peak serum concentrations occur in 30 to 60 minutes. As in leukemic pediatric patients, a wide interindividual variability in the plasma concentrations of methotrexate has been reported in pediatric patients with JRA. Following oral administration of methotrexate in doses of 6.4 to 11.2 mg/m^2/week in pediatric patients with JRA, mean serum concentrations were 0.59 micromolar (range, 0.03 to 1.40) at 1 hour, 0.44 micromolar (range, 0.01 to 1.00) at 2 hours, and 0.29 micromolar (range, 0.06 to 0.58) at 3 hours. In pediatric patients receiving methotrexate for acute lymphocytic leukemia (6.3 to 30 mg/m^2), or for JRA (3.75 to 26.2 mg/m^2), the terminal half-life has been reported to range from 0.7 to 5.8 hours or 0.9 to 2.3 hours, respectively.

Distribution - After intravenous administration, the initial volume of distribution is approximately 0.18 L/kg (18% of body weight) and steady-state volume of distribution is approximately 0.4 to 0.8 L/kg (40% to 80% of body weight). Methotrexate competes with reduced folates for active transport across cell membranes by means of a single carrier-mediated active transport process. At serum concentrations greater than 100 micromolar, passive diffusion becomes a major pathway by which effective intracellular concentrations can be achieved. Methotrexate in serum is approximately 50% protein bound. Laboratory studies demonstrate that it may be displaced from plasma albumin by various compounds including sulfonamides, salicylates, tetracyclines, chloramphenicol, and phenytoin.

Methotrexate does not penetrate the blood-cerebrospinal fluid barrier in therapeutic amounts when given orally or parenterally. High CSF concentrations of the drug may be attained by intrathecal administration.

In dogs, synovial fluid concentrations after oral dosing were higher in inflamed than uninflamed joints. Although salicylates did not interfere with this penetration, prior prednisone treatment reduced penetration into inflamed joints to the level of normal joints.

Metabolism - After absorption, methotrexate undergoes hepatic and intracellular metabolism to polyglutamated forms which can be converted back to methotrexate by hydrolase enzymes. These polyglutamates act as inhibitors of dihydrofolate reductase and thymidylate synthetase. Small amounts of methotrexate polyglutamates may remain in tissues for extended periods. The retention and prolonged drug action of these active metabolites vary among different cells, tissues and tumors. A small amount of metabolism to 7-hydroxymethotrexate may occur at doses commonly prescribed. Accumulation of this metabolite may become significant at the high doses used in osteogenic sarcoma. The aqueous solubility of 7-hydroxymethotrexate is 3 to 5 fold lower than the parent compound. Methotrexate is partially metabolized by intestinal flora after oral administration.

Half-Life - The terminal half-life reported for methotrexate is approximately three to ten hours for patients receiving treatment for psoriasis, or rheumatoid arthritis or low dose antineoplastic therapy (less than 30 mg/m^2). For patients receiving high doses of methotrexate, the terminal half-life is eight to 15 hours.

Excretion - Renal excretion is the primary route of elimination and is dependent upon dosage and route of administration. With IV administration, 80% to 90% of the administered dose is excreted unchanged in the urine within 24 hours. There is limited biliary excretion amounting to 10% or less of the administered dose. Enterohepatic recirculation of methotrexate has been proposed.

Renal excretion occurs by glomerular filtration and active tubular secretion. Nonlinear elimination due to saturation of renal tubular reabsorption has been observed in psoriatic patients at doses between 7.5 and 30 mg. Impaired renal function, as well as concurrent use of drugs such as weak organic acids that also undergo tubular secretion, can markedly increase methotrexate serum levels. Excellent correlation has been reported between methotrexate clearance and endogenous creatinine clearance.

Methotrexate clearance rates vary widely and are generally decreased at higher doses. Delayed drug clearance has been identified as one of the major factors responsible for methotrexate toxicity. It has been postulated that the toxicity of methotrexate for normal tissues is more dependent upon the duration of exposure to the drug rather than the peak level achieved. When a patient has delayed drug elimination due to compromised renal function, a third space effusion, or other causes, methotrexate serum concentrations may remain elevated for prolonged periods.

The potential for toxicity from high dose regimens or delayed excretion is reduced by the administration of leucovorin calcium during the final phase of methotrexate plasma elimination. Pharmacokinetic monitoring of methotrexate serum concentrations may help identify those patients at high risk for methotrexate toxicity and aid in proper adjustment of leucovorin dosing. Guidelines for monitoring serum methotrexate levels, and for adjustment of leucovorin dosing to reduce the risk of methotrexate toxicity, are provided below in DOSAGE AND ADMINISTRATION.

Methotrexate has been detected in human breast milk. The highest breast milk to plasma concentration ratio reached was 0.08:1.

INDICATIONS AND USAGE

Neoplastic Diseases

Methotrexate is indicated in the treatment of gestational choriocarcinoma, chorioadenoma destruens and hydatidiform mole.

Methotrexate is used in maintenance therapy in combination with other chemotherapeutic agents.

Methotrexate is used alone or in combination with other anticancer agents in the treatment of breast cancer, epidermoid cancers of the head and neck, advanced mycosis fungoides (cutaneous T cell lymphoma), and lung cancer, particularly squamous cell and small cell types. Methotrexate is also used in combination with other chemotherapeutic agents in the treatment of advanced stage non-Hodgkin’s lymphomas.

Psoriasis

Methotrexate is indicated in the symptomatic control of severe, recalcitrant, disabling psoriasis that is not adequately responsive to other forms of therapy, but only when the diagnosis has been established, as by biopsy and/or after dermatologic consultation. It is important to ensure that a psoriasis “flare” is not due to an undiagnosed concomitant disease affecting immune responses.

Rheumatoid Arthritis including Polyarticular-Course Juvenile Rheumatoid Arthritis

Methotrexate is indicated in the management of selected adults with severe, active, rheumatoid arthritis (ACR criteria), or children with active polyarticular-course juvenile rheumatoid arthritis, who have had an insufficient therapeutic response to, or are intolerant of, an adequate trial of first-line therapy including full dose non-steroidal anti-inflammatory agents (NSAIDs).

Aspirin, NSAIDs, and/or low dose steroids may be continued, although the possibility of increased toxicity with concomitant use of NSAIDs including salicylates has not been fully explored. (See PRECAUTIONS, Drug Interactions.) Steroids may be reduced gradually in patients who respond to methotrexate. Combined use of methotrexate with gold, penicillamine, hydroxychloroquine, sulfasalazine, or cytotoxic agents, has not been studied and may increase the incidence of adverse effects. Rest and physiotherapy as indicated should be continued.

CONTRAINDICATIONS

Methotrexate can cause fetal death or teratogenic effects when administered to a pregnant woman. Methotrexate is contraindicated in pregnant women with psoriasis or rheumatoid arthritis and should be used in the treatment of neoplastic diseases only when the potential benefit outweighs the risk to the fetus. Women of childbearing potential should not be started on methotrexate until pregnancy is excluded and should be fully counseled on the serious risk to the fetus (See PRECAUTIONS) should they become pregnant while undergoing treatment. Pregnancy should be avoided if either partner is receiving methotrexate; during and for a minimum of three months after therapy for male patients, and during and for at least one ovulatory cycle after therapy for female patients. (See Boxed WARNINGS.)

Because of the potential for serious adverse reactions from methotrexate in breast fed infants, it is contraindicated in nursing mothers.

Patients with psoriasis or rheumatoid arthritis with alcoholism, alcoholic liver disease or other chronic liver disease should not receive methotrexate.

Patients with psoriasis or rheumatoid arthritis who have overt or laboratory evidence of immunodeficiency syndromes should not receive methotrexate.

Patients with psoriasis or rheumatoid arthritis who have preexisting blood dyscrasias, such as bone marrow hypoplasia, leukopenia, thrombocytopenia or significant anemia, should not receive methotrexate.

Patients with a known hypersensitivity to methotrexate should not receive the drug.

WARNINGS - SEE BOXED WARNINGS.

Methotrexate formulations and diluents containing preservatives must not be used for intrathecal or high dose methotrexate therapy.

PRECAUTIONS

General

Methotrexate has the potential for serious toxicity. (See Boxed WARNINGS.) Toxic effects may be related in frequency and severity to dose or frequency of administration but have been seen at all doses. Because they can occur at any time during therapy, it is necessary to follow patients on methotrexate closely. Most adverse reactions are reversible if detected early. When such reactions do occur, the drug should be reduced in dosage or discontinued and appropriate corrective measures should be taken. If necessary, this could include the use of leucovorin calcium and/or acute, intermittent hemodialysis with a high-flux dialyzer. (See OVERDOSAGE.) If methotrexate therapy is reinstituted, it should be carried out with caution, with adequate consideration of further need for the drug and with increased alertness as to possible recurrence of toxicity.

The clinical pharmacology of methotrexate has not been well studied in older individuals. Due to diminished hepatic and renal function as well as decreased folate stores in this population, relatively low doses should be considered, and these patients should be closely monitored for early signs of toxicity.

Information for Patients

Patients should be informed of the early signs and symptoms of toxicity, of the need to see their physician promptly if they occur, and the need for close follow-up, including periodic laboratory tests to monitor toxicity.

Both the physician and pharmacist should emphasize to the patient that the recommended dose is taken weekly in rheumatoid arthritis and psoriasis, and that mistaken daily use of the recommended dose has led to fatal toxicity. Patients should be encouraged to read the Patient Instructions sheet within the Dose Pack. Prescriptions should not be written or refilled on a PRN basis.

Patients should be informed of the potential benefit and risk in the use of methotrexate. The risk of effects on reproduction should be discussed with both male and female patients taking methotrexate.

Laboratory Tests

Patients undergoing methotrexate therapy should be closely monitored so that toxic effects are detected promptly. Baseline assessment should include a complete blood count with differential and platelet counts, hepatic enzymes, renal function tests, and a chest X-ray. During therapy of rheumatoid arthritis and psoriasis, monitoring of these parameters is recommended: hematology at least monthly, renal function and liver function every 1 to 2 months. More frequent monitoring is usually indicated during antineoplastic therapy. During initial or changing doses, or during periods of increased risk of elevated methotrexate blood levels (e.g., dehydration), more frequent monitoring may also be indicated.

Transient liver function test abnormalities are observed frequently after methotrexate administration and are usually not cause for modification of methotrexate therapy. Persistent liver function test abnormalities, and/or depression of serum albumin may be indicators of serious liver toxicity and require evaluation. (See PRECAUTIONS, Organ System Toxicity,Hepatic.)

A relationship between abnormal liver function tests and fibrosis or cirrhosis of the liver has not been established for patients with psoriasis. Persistent abnormalities in liver function tests may precede appearance of fibrosis or cirrhosis in the rheumatoid arthritis population.

Pulmonary function tests may be useful if methotrexate-induced lung disease is suspected, especially if baseline measurements are available.

Drug Interactions

Concomitant administration of some NSAIDs with high dose methotrexate therapy has been reported to elevate and prolong serum methotrexate levels, resulting in deaths from severe hematologic and gastrointestinal toxicity.

Caution should be used when NSAIDs and salicylates are administered concomitantly with lower doses of methotrexate. These drugs have been reported to reduce the tubular secretion of methotrexate in an animal model and may enhance its toxicity.

Despite the potential interactions, studies of methotrexate in patients with rheumatoid arthritis have usually included concurrent use of constant dosage regimens of NSAIDs, without apparent problems. It should be appreciated, however, that the doses used in rheumatoid arthritis (7.5 to 20 mg/wk) are somewhat lower than those used in psoriasis and that larger doses could lead to unexpected toxicity.

Methotrexate is partially bound to serum albumin, and toxicity may be increased because of displacement by certain drugs, such as salicylates, phenylbutazone, phenytoin, and sulfonamides. Renal tubular transport is also diminished by probenecid; use of methotrexate with this drug should be carefully monitored.

Oral antibiotics such as tetracycline, chloramphenicol, and nonabsorbable broad spectrum antibiotics, may decrease intestinal absorption of methotrexate or interfere with the enterohepatic circulation by inhibiting bowel flora and suppressing metabolism of the drug by bacteria.

Penicillins may reduce the renal clearance of methotrexate; increased serum concentrations of methotrexate with concomitant hematologic and gastrointestinal toxicity have been observed with methotrexate. Use of methotrexate with penicillins should be carefully monitored.

The potential for increased hepatotoxicity when methotrexate is administered with other hepatotoxic agents has not been evaluated. However, hepatotoxicity has been reported in such cases. Therefore, patients receiving concomitant therapy with methotrexate and other potential hepatotoxins (e.g., azathioprine, retinoids, sulfa-salazine) should be closely monitored for possible increased risk of hepatotoxicity.

Methotrexate may decrease the clearance of theophylline; theophylline levels should be monitored when used concurrently with methotrexate.

Certain side effects such as mouth sores may be reduced by folate supplementation with methotrexate.

Trimethoprim/sulfa-methoxazole has been reported rarely to increase bone marrow suppression in patients receiving methotrexate, probably by an additive antifolate effect.

The use of nitrous oxide anesthesia potentiates the effect of methotrexate on folate-dependent metabolic pathways, resulting in the potential for increased toxicity such as stomatitis, myelosuppression, and neurotoxicity. Avoid concomitant nitrous oxide anesthesia in patients receiving methotrexate. Use caution when administering methotrexate after a recent history of nitrous oxide administration.

Carcinogenesis, Mutagenesis, and Impairment of Fertility

No controlled human data exist regarding the risk of neoplasia with methotrexate. Methotrexate has been evaluated in a number of animal studies for carcinogenic potential with inconclusive results. Although there is evidence that methotrexate causes chromosomal damage to animal somatic cells and human bone marrow cells, the clinical significance remains uncertain. Non-Hodgkin’s lymphoma and other tumors have been reported in patients receiving low-dose oral methotrexate. However, there have been instances of malignant lymphoma arising during treatment with low-dose oral methotrexate, which have regressed completely following withdrawal of methotrexate, without requiring active anti-lymphoma treatment. Benefits should be weighed against the potential risks before using methotrexate alone or in combination with other drugs, especially in pediatric patients or young adults. Methotrexate causes embryotoxicity, abortion, and fetal defects in humans. It has also been reported to cause impairment of fertility, oligospermia and menstrual dysfunction in humans, during and for a short period after cessation of therapy.

Pregnancy

Psoriasis and rheumatoid arthritis: Methotrexate is in Pregnancy Category X. See CONTRAINDICATIONS.

Nursing Mothers

See CONTRAINDICATIONS.

Pediatric Use

Safety and effectiveness in pediatric patients have been established only in cancer chemotherapy and in polyarticular-course juvenile rheumatoid arthritis.

Published clinical studies evaluating the use of methotrexate in children and adolescents (i.e., patients 2 to 16 years of age) with JRA demonstrated safety comparable to that observed in adults with rheumatoid arthritis. (See CLINICAL PHARMACOLOGY, ADVERSE REACTIONS and DOSAGE AND ADMINISTRATION.)

Geriatric Use

Clinical studies of methotrexate did not include sufficient numbers of subjects age 65 and over to determine whether they respond differently from younger subjects. In general, dose selection for an elderly patient should be cautious reflecting the greater frequency of decreased hepatic and renal function, decreased folate stores, concomitant disease or other drug therapy (i.e. that interfere with renal function, methotrexate or folate metabolism) in this population (See PRECAUTIONS, Drug Interactions.) Since decline in renal function may be associated with increases in adverse events and serum creatinine measurements may over estimate renal function in the elderly, more accurate methods (i.e., creatine clearance) should be considered. Serum methotrexate levels may also be helpful. Elderly patients should be closely monitored for early signs of hepatic, bone marrow and renal toxicity. In chronic use situations, certain toxicities may be reduced by folate supplementation. Post-marketing experience suggests that the occurrence of bone marrow suppression, thrombocytopenia, and pneumonitis may increase with age. See Boxed WARNINGS and ADVERSE REACTIONS.

Organ System Toxicity

Gastrointestinal: If vomiting, diarrhea, or stomatitis occur, which may result in dehydration, methotrexate should be discontinued until recovery occurs. Methotrexate should be used with extreme caution in the presence of peptic ulcer disease or ulcerative colitis.

Hematologic: Methotrexate can suppress hematopoiesis and cause anemia, aplastic anemia, pancytopenia, leukopenia, neutropenia, and/or thrombocytopenia. In patients with malignancy and preexisting hematopoietic impairment, the drug should be used with caution, if at all. In controlled clinical trials in rheumatoid arthritis (n=128), leukopenia (WBC <3000/mm^3) was seen in 2 patients, thrombocytopenia (platelets <100,000/mm^3) in 6 patients, and pancytopenia in 2 patients.

In psoriasis and rheumatoid arthritis, methotrexate should be stopped immediately if there is a significant drop in blood counts. In the treatment of neoplastic diseases, methotrexate should be continued only if the potential benefit warrants the risk of severe myelosuppression. Patients with profound granulocytopenia and fever should be evaluated immediately and usually require parenteral broad-spectrum antibiotic therapy.

Hepatic: Methotrexate has the potential for acute (elevated transaminases) and chronic (fibrosis and cirrhosis) hepatotoxicity. Chronic toxicity is potentially fatal; it generally has occurred after prolonged use (generally two years or more) and after a total dose of at least 1.5 grams. In studies in psoriatic patients, hepatotoxicity appeared to be a function of total cumulative dose and appeared to be enhanced by alcoholism, obesity, diabetes and advanced age. An accurate incidence rate has not been determined; the rate of progression and reversibility of lesions is not known. Special caution is indicated in the presence of preexisting liver damage or impaired hepatic function.

In psoriasis, liver function tests, including serum albumin, should be performed periodically prior to dosing but are often normal in the face of developing fibrosis or cirrhosis. These lesions may be detectable only by biopsy. The usual recommendation is to obtain a liver biopsy at 1) pretherapy or shortly after initiation of therapy (2 to 4 months), 2) a total cumulative dose of 1.5 grams, and 3) after each additional 1.0 to 1.5 grams. Moderate fibrosis or any cirrhosis normally leads to discontinuation of the drug; mild fibrosis normally suggests a repeat biopsy in 6 months. Milder histologic findings such as fatty change and low grade portal inflammation are relatively common pretherapy. Although these mild changes are usually not a reason to avoid or discontinue methotrexate therapy, the drug should be used with caution.

In rheumatoid arthritis, age at first use of methotrexate and duration of therapy have been reported as risk factors for hepatotoxicity; other risk factors, similar to those observed in psoriasis, may be present in rheumatoid arthritis but have not been confirmed to date. Persistent abnormalities in liver function tests may precede appearance of fibrosis or cirrhosis in this population. There is a combined reported experience in 217 rheumatoid arthritis patients with liver biopsies both before and during treatment (after a cumulative dose of at least 1.5 g) and in 714 patients with a biopsy only during treatment. There are 64 (7%) cases of fibrosis and 1 (0.1%) case of cirrhosis. Of the 64 cases of fibrosis, 60 were deemed mild. The reticulin stain is more sensitive for early fibrosis and its use may increase these figures. It is unknown whether even longer use will increase these risks.

Liver function tests should be performed at baseline and at 4 to 8 week intervals in patients receiving methotrexate for rheumatoid arthritis. Pretreatment liver biopsy should be performed for patients with a history of excessive alcohol consumption, persistently abnormal baseline liver function test values or chronic hepatitis B or C infection. During therapy, liver biopsy should be performed if there are persistent liver function test abnormalities or there is a decrease in serum albumin below the normal range (in the setting of well controlled rheumatoid arthritis).

If the results of a liver biopsy show mild changes (Roenigk grades I, II, IIIa), methotrexate may be continued and the patient monitored as per recommendations listed above. Methotrexate should be discontinued in any patient who displays persistently abnormal liver function tests and refuses liver biopsy or in any patient whose liver biopsy shows moderate to severe changes (Roenigk grade IIIb or IV).

Infection or Immunologic States: Methotrexate should be used with extreme caution in the presence of active infection, and is usually contraindicated in patients with overt or laboratory evidence of immunodeficiency syndromes. Immunization may be ineffective when given during methotrexate therapy. Immunization with live virus vaccines is generally not recommended. There have been reports of disseminated vaccinia infections after smallpox immunization in patients receiving methotrexate therapy.

Hypogammaglobulinemia has been reported rarely.

Potentially fatal opportunistic infections, especially Pneumocystis carinii pneumonia, may occur with methotrexate therapy. When a patient presents with pulmonary symptoms, the possibility of Pneumocystis carinii pneumonia should be considered.

Pulmonary: Pulmonary symptoms (especially a dry nonproductive cough) or a nonspecific pneumonitis occurring during methotrexate therapy may be indicative of a potentially dangerous lesion and require interruption of treatment and careful investigation. Although clinically variable, the typical patient with methotrexate induced lung disease presents with fever, cough, dyspnea, hypoxemia, and an infiltrate on chest X-ray; infection (including pneumonia) needs to be excluded. This lesion can occur at all dosages.

Renal: Methotrexate may cause renal damage that may lead to acute renal failure. Nephrotoxicity is due primarily to the precipitation of methotrexate and 7-hydroxymethotrexate in the renal tubules. Close attention to renal function including adequate hydration, urine alkalinization and measurement of serum methotrexate and creatinine levels are essential for safe administration.

Skin: Severe, occasionally fatal, dermatologic reactions, including toxic epidermal necrolysis, Stevens-Johnson syndrome, exfoliative dermatitis, skin necrosis, and erythema multiforme, have been reported in children and adults, within days of oral, intramuscular, intravenous, or intrathecal methotrexate administration. Reactions were noted after single or multiple, low, intermediate or high doses of methotrexate in patients with neoplastic and non-neoplastic diseases.

Other Precautions: Methotrexate should be used with extreme caution in the presence of debility.

Methotrexate exits slowly from third space compartments (e.g., pleural effusions or ascites). This results in a prolonged terminal plasma half-life and unexpected toxicity. In patients with significant third space accumulations, it is advisable to evacuate the fluid before treatment and to monitor plasma methotrexate levels.

Lesions of psoriasis may be aggravated by concomitant exposure to ultraviolet radiation. Radiation dermatitis and sunburn may be “recalled” by the use of methotrexate.

ADVERSE REACTIONS

IN GENERAL, THE INCIDENCE AND SEVERITY OF ACUTE SIDE EFFECTS ARE RELATED TO DOSE AND FREQUENCY OF ADMINISTRATION. THE MOST SERIOUS REACTIONS ARE DISCUSSED ABOVE UNDER ORGAN SYSTEM TOXICITY IN THE PRECAUTION SECTION. THAT SECTION SHOULD ALSO BE CONSULTED WHEN LOOKING FOR INFORMATION ABOUT ADVERSE REACTIONS WITH METHOTREXATE.

The most frequently reported adverse reactions include ulcerative stomatitis, leukopenia, nausea, and abdominal distress. Other frequently reported adverse effects are malaise, undue fatigue, chills and fever, dizziness and decreased resistance to infection.

Other adverse reactions that have been reported with methotrexate are listed below by organ system. In the oncology setting, concomitant treatment and the underlying disease make specific attribution of a reaction to methotrexate difficult.

Alimentary System: gingivitis, pharyngitis, stomatitis, anorexia, nausea, vomiting, diarrhea, hematemesis, melena, gastrointestinal ulceration and bleeding, enteritis, pancreatitis.

Blood and Lymphatic System Disorders: suppressed hematopoiesis causing anemia, aplastic anemia, pancytopenia, leukopenia, neutropenia and/or thrombocytopenia, lymphadenopathy and lymphoproliferative disorders (including reversible). Hypogammaglobulinemia has been reported rarely.

Cardiovascular: pericarditis, pericardial effusion, hypotension, and thromboembolic events (including arterial thrombosis, cerebral thrombosis, deep vein thrombosis, retinal vein thrombosis, thrombophlebitis, and pulmonary embolus).

Central Nervous System: headaches, drowsiness, blurred vision, transient blindness, speech impairment including dysarthria and aphasia, hemiparesis, paresis and convulsions have also occurred following administration of methotrexate. Following low doses, there have been occasional reports of transient subtle cognitive dysfunction, mood alteration, unusual cranial sensations, leukoencephalopathy, or encephalopathy.

Hepatobiliary: disorders, hepatotoxicity, acute hepatitis, chronic fibrosis and cirrhosis, decrease in serum albumin, liver enzyme elevations.

Infection: There have been case reports of sometimes fatal opportunistic infections in patients receiving methotrexate therapy for neoplastic and non-neoplastic diseases. Pneumocystis carinii pneumonia was the most common opportunistic infection. There have also been reports of infections, pneumonia, sepsis, nocardiosis, histoplasmosis, cryptococcosis, herpes zoster, H. simplex hepatitis, and disseminated H. simplex.

Musculoskeletal System: stress fracture.

Ophthalmic: conjunctivitis, serious visual changes of unknown etiology.

Pulmonary System: respiratory fibrosis, respiratory failure, interstitial pneumonitis; deaths have been reported, and chronic interstitial obstructive pulmonary disease has occasionally occurred.

Skin: erythematous rashes, pruritus, urticaria, photosensitivity, pigmentary changes, alopecia, ecchymosis, telangiectasia, acne, furunculosis, erythema multiforme, toxic epidermal necrolysis, Stevens-Johnson syndrome, skin necrosis, skin ulceration, and exfoliative dermatitis.

Urogenital System: severe nephropathy or renal failure, azotemia, cystitis, hematuria; defective oogenesis or spermatogenesis, transient oligospermia, menstrual dysfunction, vaginal discharge, and gynecomastia; infertility, abortion, fetal defects.

Other rarer reactions related to or attributed to the use of methotrexate such as nodulosis, vasculitis, arthralgia/myalgia, loss of libido/impotence, diabetes, osteoporosis, sudden death, reversible lymphomas, tumor lysis syndrome, soft tissue necrosis and osteonecrosis. Anaphylactoid reactions have been reported.

Adverse Reactions in Double-Blind Rheumatoid Arthritis Studies

The approximate incidences of methotrexate attributed (i.e., placebo rate subtracted) adverse reactions in 12 to 18 week double-blind studies of patients (n=128) with rheumatoid arthritis treated with low-dose oral (7.5 to 15 mg/week) pulse methotrexate, are listed below. Virtually all of these patients were on concomitant nonsteroidal anti-inflammatory drugs and some were also taking low dosages of corticosteroids. Hepatic histology was not examined in these short-term studies. (See PRECAUTIONS.)

Incidence greater than 10%:Elevated liver function tests 15%, nausea/vomiting 10%.

Incidence 3% to 10%:Stomatitis, thrombocytopenia, (platelet count less than 100,000/mm^3).

Incidence 1% to 3%:Rash/pruritus/dermatitis, diarrhea, alopecia, leukopenia (WBC less than 3000/mm^3), pancytopenia, dizziness.

Two other controlled trials of patients (n=680) with Rheumatoid Arthritis on 7.5 mg to 15 mg/wk oral doses showed an incidence of interstitial pneumonitis of 1%. (See PRECAUTIONS.)

Other less common reactions included decreased hematocrit, headache, upper respiratory infection, anorexia, arthralgias, chest pain, coughing, dysuria, eye discomfort, epistaxis, fever, infection, sweating, tinnitus, and vaginal discharge.

Adverse Reactions in Psoriasis

There are no recent placebo-controlled trials in patients with psoriasis. There are two literature reports (Roenigk, 1969 and Nyfors, 1978) describing large series (n=204, 248) of psoriasis patients treated with methotrexate. Dosages ranged up to 25 mg per week and treatment was administered for up to four years. With the exception of alopecia, photosensitivity, and “burning of skin lesions” (each 3% to 10%), the adverse reaction rates in these reports were very similar to those in the rheumatoid arthritis studies. Rarely, painful plaque erosions may appear.

Adverse Reactions in JRA Studies

The approximate incidences of adverse reactions reported in pediatric patients with JRA treated with oral, weekly doses of methotrexate (5 to 20 mg/m^2/wk or 0.1 to 0.65 mg/kg/wk) were as follows (virtually all patients were receiving concomitant nonsteroidal anti-inflammatory drugs, and some also were taking low doses of cortico-steroids): elevated liver function tests, 14%; gastrointestinal reactions (e.g., nausea, vomiting, diarrhea), 11%; stomatitis, 2%; leukopenia, 2%; headache, 1.2%; alopecia, 0.5%; dizziness, 0.2%; and rash, 0.2%. Although there is experience with dosing up to 30 mg/m^2/wk in JRA, the published data for doses above 20 mg/m^2/wk are too limited to provide reliable estimates of adverse reaction rates.

OVERDOSAGE

Leucovorin is indicated to diminish the toxicity and counteract the effect of inadvertently administered overdosages of methotrexate. Leucovorin administration should begin as promptly as possible. As the time interval between methotrexate administration and leucovorin initiation increases, the effectiveness of leucovorin in counteracting toxicity decreases. Monitoring of the serum methotrexate concentration is essential in determining the optimal dose and duration of treatment with leucovorin.

In cases of massive overdosage, hydration and urinary alkalinization may be necessary to prevent the precipitation of methotrexate and/or its metabolites in the renal tubules. Generally speaking, neither hemodialysis nor peritoneal dialysis has been shown to improve methotrexate elimination. However, effective clearance of methotrexate has been reported with acute, intermittent hemodialysis using a high-flux dialyzer (Wall, SM et al: Am J Kidney Dis28(6): 846-854, 1996).

In postmarketing experience, overdose with methotrexate has generally occurred with oral and intrathecal administration, although intravenous and intramuscular overdose have also been reported.

Reports of oral overdose often indicate accidental daily administration instead of weekly (single or divided doses). Symptoms commonly reported following oral overdose include those symptoms and signs reported at pharmacologic doses, particularly hematologic and gastrointestinal reaction. For example, leukopenia, thrombocytopenia, anemia, pancytopenia, bone marrow suppression, mucositis, stomatitis, oral ulceration, nausea, vomiting, gastrointestinal ulceration, gastrointestinal bleeding. In some cases, no symptoms were reported. There have been reports of death following overdose. In these cases, events such as sepsis or septic shock, renal failure, and aplastic anemia were also reported.

DOSAGE AND ADMINISTRATION

Neoplastic Diseases

Oral administration in tablet form is often preferred when low doses are being administered since absorption is rapid and effective serum levels are obtained.

Choriocarcinoma and similar trophoblastic diseases: Methotrexate is administered orally or intramuscularly in doses of 15 to 30 mg daily for a five-day course. Such courses are usually repeated for 3 to 5 times as required, with rest periods of one or more weeks interposed between courses, until any manifesting toxic symptoms subside. The effectiveness of therapy is ordinarily evaluated by 24 hour quantitative analysis of urinary chorionic gonadotropin (hCG), which should return to normal or less than 50 IU/24 hr usually after the third or fourth course and usually be followed by a complete resolution of measurable lesions in 4 to 6 weeks. One to two courses of methotrexate after normalization of hCG is usually recommended. Before each course of the drug careful clinical assessment is essential. Cyclic combination therapy of methotrexate with other antitumor drugs has been reported as being useful.

Since hydatidiform mole may precede choriocarcinoma, prophylactic chemotherapy with methotrexate has been recommended.

Chorioadenoma destruens is considered to be an invasive form of hydatidiform mole. Methotrexate is administered in these disease states in doses similar to those recommended for choriocarcinoma.

Leukemia: Acute lymphoblastic leukemia in pediatric patients and young adolescents is the most responsive to present day chemotherapy. In young adults and older patients, clinical remission is more difficult to obtain and early relapse is more common.

Methotrexate alone or in combination with steroids was used initially for induction of remission in acute lymphoblastic leukemias. More recently corticosteroid therapy, in combination with other antileukemic drugs or in cyclic combinations with methotrexate included, has appeared to produce rapid and effective remissions. When used for induction, methotrexate in doses of 3.3 mg/m^2 in combination with 60 mg/m^2 of prednisone, given daily, produced remissions in 50% of patients treated, usually within a period of 4 to 6 weeks. Methotrexate in combination with other agents appears to be the drug of choice for securing maintenance of drug-induced remissions. When remission is achieved and supportive care has produced general clinical improvement, maintenance therapy is initiated, as follows: Methotrexate is administered 2 times weekly either by mouth or intramuscularly in total weekly doses of 30 mg/m^2. It has also been given in doses of 2.5 mg/kg intravenously every 14 days. If and when relapse does occur, reinduction of remission can again usually be obtained by repeating the initial induction regimen.

A variety of combination chemotherapy regimens have been used for both induction and maintenance therapy in acute lymphoblastic leukemia. The physician should be familiar with the new advances in antileukemic therapy.

Lymphomas: In Burkitt’s tumor, Stages I-II, methotrexate has produced prolonged remissions in some cases. Recommended dosage is 10 to 25 mg/day orally for 4 to 8 days. In Stage III, methotrexate is commonly given concomitantly with other anti-tumor agents. Treatment in all stages usually consists of several courses of the drug interposed with 7 to 10 day rest periods. Lymphosarcomas in Stage III may respond to combined drug therapy with methotrexate given in doses of 0.625 to 2.5 mg/kg daily.

Mycosis Fungoides (cutaneous T cell lymphoma): Therapy with methotrexate as a single agent appears to produce clinical responses in up to 50% of patients treated. Dosage in early stages is usually 5 to 50 mg once weekly. Dose reduction or cessation is guided by patient response and hematologic monitoring. Methotrexate has also been administered twice weekly in doses ranging from 15 to 37.5 mg in patients who have responded poorly to weekly therapy.

Psoriasis, Rheumatoid Arthritis, and Juvenile Rheumatoid Arthritis

Adult Rheumatoid Arthritis: Recommended Starting Dosage Schedules

1. Single oral doses of 7.5 mg once weekly.

2. Divided oral dosages of 2.5 mg at 12 hour intervals for 3 doses given as a course once weekly.

Polyarticular-Course Juvenile Rheumatoid Arthritis: The recommended starting dose is 10 mg/m^2 given once weekly.

For either adult RA or polyarticular-course JRA dosages may be adjusted gradually to achieve an optimal response. Limited experience shows a significant increase in the incidence and severity of serious toxic reactions, especially bone marrow suppression, at doses greater than 20 mg/wk in adults. Although there is experience with doses up to 30 mg/m^2/wk in children, there are too few published data to assess how doses over 20 mg/m^2/wk might affect the risk of serious toxicity in children. Experience does suggest, however, that children receiving 20 to 30 mg/m^2/wk (0.65 to 1.0 mg/kg/wk) may have better absorption and fewer gastrointestinal side effects if methotrexate is administered either intramuscularly or subcutaneously.

Therapeutic response usually begins within 3 to 6 weeks and the patient may continue to improve for another 12 weeks or more.

The optimal duration of therapy is unknown. Limited data available from long-term studies in adults indicate that the initial clinical improvement is maintained for at least two years with continued therapy. When methotrexate is discontinued, the arthritis usually worsens within 3 to 6 weeks.

The patient should be fully informed of the risks involved and should be under constant supervision of the physician. (See Information for Patients under PRECAUTIONS.) Assessment of hematologic, hepatic, renal, and pulmonary function should be made by history, physical examination, and laboratory tests before beginning, periodically during, and before reinstituting methotrexate therapy. (See PRECAUTIONS.) Appropriate steps should be taken to avoid conception during methotrexate therapy. (See PRECAUTIONS and CONTRAINDICATIONS.)

All schedules should be continually tailored to the individual patient. An initial test dose may be given prior to the regular dosing schedule to detect any extreme sensitivity to adverse effects. (See ADVERSE REACTIONS.) Maximal myelosuppression usually occurs in seven to ten days.

Psoriasis: Recommended Starting Dose Schedules

1. Weekly single oral, IM or IV dose schedule: 10 to 25 mg per week until adequate response is achieved.

2. Divided oral dose schedule: 2.5 mg at 12-hour intervals for three doses.

Dosages in each schedule may be gradually adjusted to achieve optimal clinical response; 30 mg/week should not ordinarily be exceeded.

Once optimal clinical response has been achieved, each dosage schedule should be reduced to the lowest possible amount of drug and to the longest possible rest period. The use of methotrexate may permit the return to conventional topical therapy, which should be encouraged.

HANDLING AND DISPOSAL

Procedures for proper handling and disposal of anticancer drugs should be considered. Several guidelines on this subject have been published.^1-5 There is no general agreement that all of the procedures recommended in the guidelines are necessary or appropriate.

HOW SUPPLIED

Product: 50090-2345

NDC: 50090-2345-9 36 TABLET in a BOTTLE

REFERENCES

1. Controlling occupational exposure to hazardous drugs (OSHA Work-Practice Guidelines). Am J Health Syst Pharm 1996; 53: 1669-1685.

2. National Study Commission on Cytotoxic Exposure - Recommendations for Handling Cytotoxic Agents. Available from Louis P. Jeffrey, Sc D, Chairman, National Study Commission on Cytotoxic Exposure, Massachusetts College of Pharmacy and Allied Health Sciences, 179 Longwood Avenue, Boston, Massachusetts 02115.

3. Clinical Oncological Society of Australia: Guidelines and recommendations for safe handling of antineoplastic agents. Med J Australia 1983; 1:426-428.

4. Jones RB, et al. Safe handling of chemotherapeutic agents: A report from the Mount Sinai Medical Center. CA - A Cancer Journal for Clinicians Sept/Oct 1983; 258-263.

5. American Society of Hospital Pharmacists technical assistance bulletin on handling cytotoxic and hazardous drugs. Am J Hosp Pharm 1990; 47:1033-1049.

TEVA PHARMACEUTICALS USA, INC.
North Wales, PA 19454

Rev. C 3/2018

Patient Information

Methotrexate (meth” oh trex’ ate) Tablets USP

Read the Patient Instructions that come with methotrexate before you start using it and each time you get a refill. There may be new information. This leaflet does not take the place of talking with your doctor about your condition.

What is the most important information I should know about methotrexate?

- Methotrexate can cause serious side effects that may be life threatening (see "What are the possible or reasonably likely side effects of methotrexate?"). Most side effects can be found by medical tests before they become serious. Your doctor may do regular tests to check how methotrexate is affecting your body. It is important that you stay under a doctor's care while taking methotrexate. Call your doctor right away to report any side effects or symptoms you get.
- Methotrexate can cause birth defects or death of an unborn child. Therefore, if you are pregnant or your sexual partner is pregnant, or plans to become pregnant, do not take methotrexate. Neither you nor your partner should become pregnant while taking methotrexate. Women should wait at least 1 menstrual cycle after stopping treatment with methotrexate before getting pregnant. Men should wait at least 3 months after stopping treatment with methotrexate before getting their partner pregnant. Women who can become pregnant should have a pregnancy test before starting methotrexate. During treatment with methotrexate men whose partners and women who are able to get pregnant should use effective birth control.

What is methotrexate?

Methotrexate is a prescription medicine used in treating certain cancers, severe rheumatoid arthritis including polyarticular juvenile rheumatoid arthritis, and severe psoriasis.

Who should not take methotrexate?

Do not take methotrexate if:

- you are pregnant or planning to become pregnant. Methotrexate can cause birth defects or death to your unborn child. See ‘What is the most important information I should know about methotrexate?”
- you are breastfeeding. Methotrexate can harm your baby. You will need to decide either to breastfeed or to take methotrexate, but not both.
- you have any conditions that weaken your immune system (immunodeficiency conditions).
- your bone marrow does not make enough blood cells, or if you have low white blood cell counts, low platelet counts, or serious anemia.
- you drink alcohol or have liver problems from alcohol abuse.
- you have chronic liver disease.
- you are allergic to methotrexate or any of the ingredients in methotrexate. See the end of this leaflet for a complete list of ingredients in methotrexate.

Before using methotrexate tell your doctor:

- about all your medical problems including if you:
- have kidney problems or are getting dialysis treatments
- have liver problems
- have fluid in your stomach area (ascites)
- have lung problems or fluid in your lungs (pleural effusion)
- about all the medicines you take including prescription and nonprescription medicines, vitamins and herbal supplements. Methotrexate and certain other medicines can affect each other and cause serious side effects. Do not start or change any medicines unless you have talked to your doctor and your doctor has told you it is safe. Know all the medicines that you take and keep a list of them with you at all times to show doctors and pharmacists.

How should I take methotrexate?

- Take methotrexate exactly as prescribed by your doctor. Your dose of methotrexate and when you take it will depend on the condition that is being treated. Do not take more methotrexate than prescribed. Do not change your dose of methotrexate unless your doctor has told you to. For treatment of severe psoriasis, and severe rheumatoid arthritis including juvenile rheumatoid arthritis, methotrexate should be taken weekly, not every day. This weekly dose is taken either at one time or in several doses.
- If you miss a dose of methotrexate call your doctor to ask if you should take the dose or not.
- If you take too much methotrexate call your doctor or go to your nearest emergency room right away. You will need to take a medicine called an antidote as soon as possible.
- Call your doctor right away for further instructions if you get dehydrated (lose a large amount of body fluids). This can happen if you are sick and have a fever, vomiting, or diarrhea. Dehydration can also happen when you sweat a lot with activities or exercise and don't drink enough fluids.
- Stop taking methotrexate if you get diarrhea, or if you get sores in your mouth. Call your doctor right away. If you keep taking methotrexate with these symptoms, you could get serious bleeding or tearing of your digestive tract.
- Your doctor should do regular tests to monitor how methotrexate is affecting your body. Check with your doctor after having any blood tests before taking methotrexate again. Your doctor will tell you if it is safe to take more methotrexate.
- Certain side effects such as mouth sores may be reduced by folate supplementation with methotrexate.

What should I avoid while taking methotrexate?

Do not:

- get pregnant or try to become pregnant. See “What is the most important information I should know about methotrexate?”
- breastfeed. See "Who should not take methotrexate?"
- drink alcohol. Alcohol drinks, including beer and wine, may increase some of the side effects with methotrexate, including the chance of liver damage.
- take certain live virus vaccines.

What are the possible or reasonably likely side effects of methotrexate?

Methotrexate can cause serious and life-threatening problems including (see “What is the most important information I should know about methotrexate”?):

- birth defects and death of an unborn child
- serious anemia, lower white cells, red cells, and platelets in your blood
- liver damage
- kidney damage
- lung disease
- cancer of the lymph system (lymphoma)
- severe skin reactions and rashes
- opportunistic infections such as Pneumocystis carinii pneumonia
- soft tissue and bone damage if you are getting radiation therapy at the same time you are taking methotrexate

The most common side effects of methotrexate include:

- mouth sores
- low white blood cells
- nausea, upset stomach
- feeling poorly
- tiredness, chills, fever, dizziness
- higher chance for getting infections
- diarrhea
- vomiting
- hair loss
- easy bruising

Stop taking methotrexate and call your doctor right away if you get diarrhea, mouth sores, a fever, dehydration, cough, bleeding, shortness of breath, any signs of infection, or a skin rash. If you have any questions about these or other side effects, talk to your doctor. These are not all the side effects of methotrexate. Ask your doctor or pharmacist for more information.

Call your doctor for medical advice about side effects. You may report side effects to FDA at 1-800-FDA-1088.

How should I store methotrexate?

- Store methotrexate at room temperature between 68° to 77°F (20° to 25°C).
- Keep methotrexate away from light.
- Keep methotrexate and all medicines out of the reach of children.

General information about methotrexate tablets

Medicines are sometimes prescribed for purposes other than those listed in a Patient Information leaflet. Do not use methotrexate for a condition for which it was not prescribed. Do not give methotrexate to other people, even if they have the same symptoms that you have. It may harm them.

This leaflet summaries the most important information about methotrexate. If you would like more information, talk with your doctor. You can ask your doctor or pharmacist for information about methotrexate that is written for healthcare professionals.

For additional information, please contact TEVA PHARMACEUTICALS USA, INC. at our toll-free number: 1-888-838-2872.

What are the ingredients in methotrexate?

Active Ingredient: methotrexate sodium

Inactive Ingredients: hydroxypropyl methylcellulose, lactose anhydrous, magnesium stearate, microcrystalline cellulose, polyethylene glycol, pregelatinized corn starch, propylene glycol, sodium carbonate monohydrate and talc.

TEVA PHARMACEUTICALS USA, INC.
North Wales, PA 19454

This Patient Information has been approved by the U.S. Food and Drug Administration. Iss. 2/2016

Storage

Store at 20° to 25°C (68° to 77°F) [See USP Controlled Room Temperature]. Protect from light.